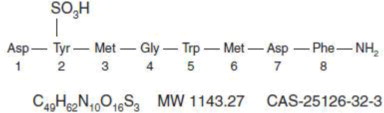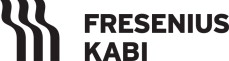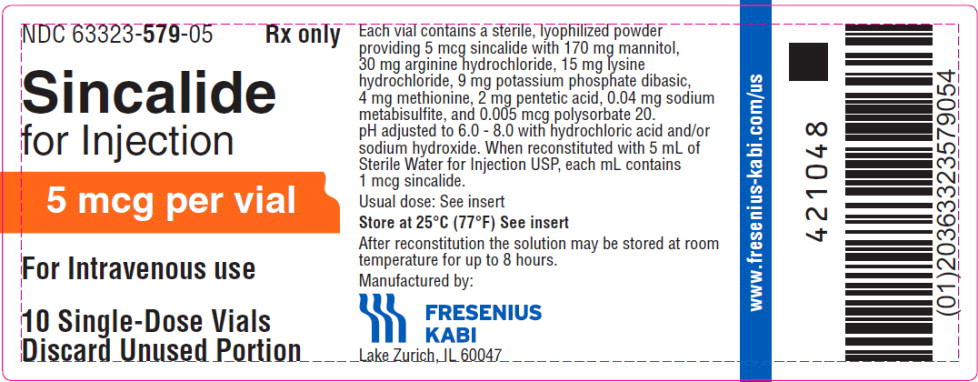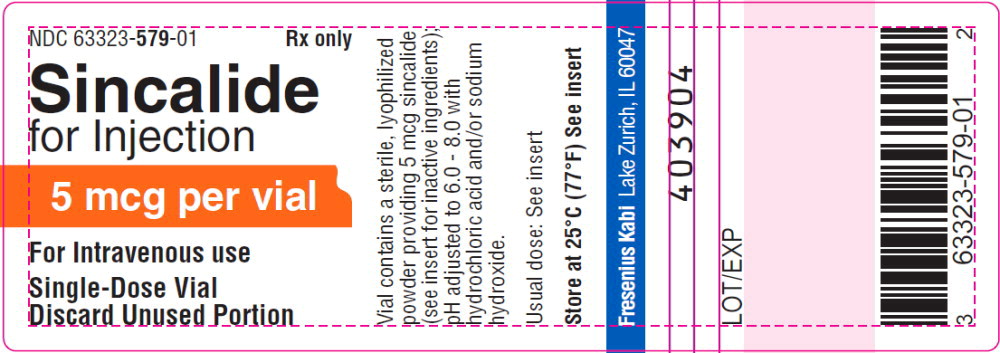 DRUG LABEL: SINCALIDE

NDC: 63323-579 | Form: INJECTION, POWDER, LYOPHILIZED, FOR SOLUTION
Manufacturer: Fresenius Kabi USA, LLC

Category: prescription | Type: HUMAN PRESCRIPTION DRUG LABEL
Date: 20240126

ACTIVE INGREDIENTS: Sincalide
 5 ug/5 mL
INACTIVE INGREDIENTS: mannitol 170 mg/5 mL; arginine hydrochloride 30 mg/5 mL; lysine hydrochloride 15 mg/5 mL; potassium phosphate, dibasic 9 mg/5 mL; methionine 4 mg/5 mL; sodium metabisulfite 0.04 mg/5 mL; polysorbate 20 0.005 ug/5 mL

HIGHLIGHTS OF PRESCRIBING INFORMATION

These highlights do not include all the information needed to use
SINCALIDE FOR INJECTION safely and effectively. See full prescribing information for SINCALIDE FOR INJECTION
SINCALIDE for injection, for intravenous use
Initial U.S. Approval: 1976

RECENT MAJOR CHANGES

Contraindications (4) | 10/2023
Warnings and Precautions (5.1) | 10/2023
Anaphylaxis, Anaphylactic Shock and Other Serious Hypersensitivity Reactions (5.1)

1 INDICATIONS AND USAGE

Sincalide for Injection is a cholecystokinin (CCK) analog indicated in adults to:

- stimulate gallbladder contraction, as may be assessed by various methods of diagnostic imaging, or to obtain by duodenal aspiration a sample of concentrated bile for analysis of cholesterol, bile salts, phospholipids, and crystals. (1)
- stimulate pancreatic secretion in combination with secretin prior to obtaining a duodenal aspirate for analysis of enzyme activity, composition, and cytology. (1)
- accelerate the transit of a barium meal through the small bowel, thereby decreasing the time and extent of radiation associated with fluoroscopy and x-ray examination of the intestinal tract. (1)

2 DOSAGE AND ADMINISTRATION

Recommended Adult Dosage and Administration by Indication:

To Stimulate Contraction of the Gallbladder

- 0.02 mcg/kg as a single dose over 30 to 60 seconds via intravenous injection. If satisfactory contraction does not occur in 15 minutes, administer a dose of 0.04 mcg/kg over 30 to 60 seconds. (2.1)
- Alternatively consider an intravenous infusion to reduce gastrointestinal adverse reactions: 0.12 mcg/kg diluted in 100 mL of 0.9% Sodium Chloride Injection USP and infused over 50 minutes at a rate of 2 mL per minute. (2.1, 2.2, 5.3)

To Stimulate Pancreatic Secretion in Combination with Secretin

- 30 minutes after initiation of secretin for injection, administer 0.02 mcg/kg diluted in 30 mL of 0.9% Sodium Chloride Injection USP and infused over 30 minutes at a rate of 1 mL per minute. (2.1, 2.2)

To Accelerate Transit of a Barium Meal Through the Small Intestine

- After the barium meal is beyond the proximal jejunum, administer 0.04 mcg/kg over 30 to 60 seconds via intravenous injection. (2.1)
- If satisfactory transit of the barium meal has not occurred in 30 minutes, administer a second dose of 0.04 mcg/kg over 30 to 60 seconds. (2.1)
- Alternatively consider an intravenous infusion to reduce gastrointestinal adverse reactions: 0.12 mcg/kg diluted in 100 mL 0.9% Sodium Chloride Injection USP and infused over 30 minutes. (2.1, 2.2, 5.3)

3 DOSAGE FORMS AND STRENGTHS

For injection: 5 mcg of sincalide as a lyophilized powder in a single-dose vial for reconstitution (3)

4 CONTRAINDICATIONS

- History of hypersensitivity to sulfites or sincalide. (4, 5.1)
- Intestinal obstruction. (4)

5 WARNINGS AND PRECAUTIONS

- Anaphylaxis, Anaphylactic Shock and Other Serious Hypersensitivity Reactions: Contains sodium metabisulfite. Serious reactions may occur during or soon after administration. If symptoms occur, discontinue the drug. (4, 5.1)
- Evacuation of Gallstones: Stimulation of gallbladder contraction in patients with small gallbladder stones could lead to the evacuation of the stones from the gallbladder, resulting in their lodging in the cystic duct or in the common bile duct. (5.2)
- Gastrointestinal Adverse Reactions with Intravenous Injection: Administration as an intravenous injection may cause transient nausea, vomiting, abdominal pain or cramping, dizziness or flushing. To reduce the risk of adverse reactions when used to stimulate contraction of the gallbladder or accelerate transit of a barium meal through the small intestine, administer as an intravenous infusion over 50 or 30 minutes, respectively. (2.1, 5.3)
- Preterm Labor or Spontaneous Abortion: Advise pregnant women of the potential risk for preterm labor and spontaneous abortion. (5.4, 8.1)

6 ADVERSE REACTIONS

Most common adverse reactions (≥20%) are: abdominal discomfort or pain, and nausea. (6)

To report SUSPECTED ADVERSE REACTIONS, contact Fresenius Kabi USA, LLC at 1-800-551-7176 or FDA at 1-800-FDA-1088 or www.fda.gov/medwatch.

7 DRUG INTERACTIONS

Drugs that Affect Gallbladder Motility or Contractile Response: May interfere with response to sincalide. Consider discontinuing these drugs prior to administration of Sincalide for Injection, when used to stimulate contraction of the gallbladder. (7.1)

FULL PRESCRIBING INFORMATION

1 INDICATIONS AND USAGE

Sincalide for Injection is indicated in adults to:

- to stimulate gallbladder contraction, as may be assessed by various methods of diagnostic imaging, or to obtain by duodenal aspiration a sample of concentrated bile for analysis of cholesterol, bile salts, phospholipids, and crystals;
- to stimulate pancreatic secretion in combination with secretin prior to obtaining a duodenal aspirate for analysis of enzyme activity, composition, and cytology;
- to accelerate the transit of a barium meal through the small bowel, thereby decreasing the time and extent of radiation associated with fluoroscopy and x-ray examination of the intestinal tract.

2 DOSAGE AND ADMINISTRATION

2.1 Recommended Dosage and Administration Instructions

The recommended dosage and administration of Sincalide for Injection by indication is shown in Table 1. For preparation instructions see Dosage and Administration (2.2).

Table 1: Recommended Adult Dosage and Administration of Sincalide for Injection by Treatment Indication
Indication | Recommended Adult Dosage and Administration of Sincalide for Injection
To stimulate contraction of the gallbladder | Sincalide for Injection 0.02 mcg/kg as a single dose over 30 to 60 seconds via intravenous injection. If satisfactory contraction does not occur in 15 minutes, administer a dose of 0.04 mcg/kg over 30 to 60 seconds. Alternatively, Consider an Intravenous Infusion to Reduce Gastrointestinal Adverse Reactions [see Warnings and Precautions (5.3)]: 0.12 mcg/kg diluted in 100 mL of 0.9% Sodium Chloride Injection USP and infused over 50 minutes at a rate of 2 mL per minute.
To stimulate pancreatic secretion in combination with secretin for injection | Secretin for Injection: 0.25 units/kg as intravenous infusion over 60 minutes Sincalide for Injection: 30 minutes after initiation of secretin infusion, administer Sincalide for Injection 0.02 mcg/kg diluted in 30 mL of 0.9% Sodium Chloride Injection USP and infused over 30 minutes at a rate of 1 mL per minute.
To accelerate the transit of a barium meal through the small intestine | After the barium meal is beyond the proximal jejunum, administer Sincalide for Injection 0.04 mcg/kg over 30 to 60 seconds via intravenous injection. If satisfactory transit of the barium meal has not occurred in 30 minutes, administer a second dose of 0.04 mcg/kg over 30 to 60 seconds. Alternatively, Consider an Intravenous Infusion to Reduce Gastrointestinal Adverse Reactions [see Warnings and Precautions (5.3)]: 0.12 mcg/kg diluted in 100 mL 0.9% Sodium Chloride Injection USP and infused over 30 minutes.

2.2 Preparation Instructions

For Intravenous Injection

- Reconstitute Sincalide for Injection aseptically by adding 5 mL of Sterile Water for Injection USP to the vial.
- Inspect the reconstituted solution visually for particulate matter and discoloration after reconstitution and prior to administration.
- Withdraw the prescribed dose of the reconstituted solution from the vial and administer as an intravenous injection over 30 to 60 seconds, as shown in Table 1. Discard the unused portion.
- Store the reconstituted solution at room temperature. Discard after 8 hours.
- For single use only; discard unused portion.

For Intravenous Infusion

- Reconstitute Sincalide for Injection aseptically by adding 5 mL of Sterile Water for Injection USP to the vial.
- After reconstitution, withdraw the prescribed dose of the solution from the vial. Discard unused portion.
- Dilute the reconstituted solution in 30 mL or 100 mL of 0.9% Sodium Chloride Injection USP, depending on the indication, as described in Table 1.
- Inspect the Sincalide for Injection solutions visually for particulate matter and discoloration after reconstitution, dilution and prior to administration.
- Store the diluted solution at room temperature. Discard after 1 hour.

3 DOSAGE FORMS AND STRENGTHS

For injection: 5 mcg of sincalide as a lyophilized white powder for reconstitution in a single-dose vial.

4 CONTRAINDICATIONS

Sincalide for Injection is contraindicated in patients with:

- a history of hypersensitivity to sulfites or sincalide. Serious hypersensitivity reactions have included anaphylaxis and anaphylactic shock [see Warnings and Precautions (5.1), Adverse Reactions (6)].
- intestinal obstruction.

5 WARNINGS AND PRECAUTIONS

5.1 Anaphylaxis, Anaphylactic Shock and Other Serious Hypersensitivity Reactions

Contains sodium metabisulfite [see Description (11)], a sulfite that may cause allergic-type reactions including anaphylactic symptoms and life-threatening or less severe asthmatic episodes in certain susceptible people. The overall prevalence of sulfite sensitivity in the general population is unknown and probably low. Sulfite sensitivity is seen more frequently in asthmatic than in non-asthmatic people.

In postmarketing experience, anaphylaxis, anaphylactic shock and other serious hypersensitivity reactions have been reported during and within one hour following administration of Sincalide for Injection [see Adverse Reactions (6)].

Sincalide for Injection is contraindicated in patients with a history of hypersensitivity to sulfites. Due to the potential for anaphylaxis, appropriate medical support should be readily available when Sincalide for Injection is administered. If anaphylaxis or other hypersensitivity reactions occur, immediately discontinue the infusion and initiate appropriate medical treatment. Observe patients closely during and after the infusion. Do not reinitiate Sincalide for Injection in patients who have experienced symptoms of hypersensitivity [see Contraindications (4)].

5.2 Evacuation of Gallstones

Stimulation of gallbladder contraction in patients with small gallbladder stones could lead to the evacuation of the stones from the gallbladder, resulting in their lodging in the cystic duct or in the common bile duct.

5.3 Gastrointestinal Adverse Reactions with Intravenous Injection

Administration of Sincalide for Injection as an intravenous injection may cause adverse reactions such as nausea, vomiting, abdominal pain or cramping, dizziness, and flushing [see Adverse Reactions (6)]. These reactions are generally transient. To reduce the risk of adverse reactions with intravenous injection when used to stimulate contraction of the gallbladder or accelerate transit of a barium meal through the small intestine, administer Sincalide for Injection as an intravenous infusion over 50 or 30 minutes, respectively [see Dosage and Administration (2.1)].

5.4 Preterm Labor or Spontaneous Abortion

Because of Sincalide for Injection's effect on smooth muscle, pregnant patients should be advised that spontaneous abortion or premature induction of labor may occur [see Use in Specific Populations (8.1)].

6 ADVERSE REACTIONS

The following clinically significant adverse reactions are described elsewhere in labeling:

- Anaphylaxis, anaphylactic shock, and other serious hypersensitivity reactions [see Warnings and Precautions (5.1)]
- Evacuation of gallstones [see Warnings and Precautions (5.2)]
- Adverse reactions with intravenous injection [see Warnings and Precautions (5.3)]
- Preterm labor or spontaneous abortion [see Warnings and Precautions (5.4)]

The following adverse reactions associated with the use of Sincalide for Injection were identified in clinical trials or postmarketing reports. Because these reactions were reported voluntarily from a population of uncertain size, it is not always possible to estimate their frequency, reliably, or to establish a causal relationship to drug exposure.

The most frequent adverse reactions (20% or greater) are gastrointestinal: abdominal discomfort or pain, and nausea; these may not necessarily indicate an abnormality of the biliary tract unless there is other clinical or radiologic evidence of disease.

Less common adverse reactions include:

Hypersensitivity reactions: anaphylaxis and anaphylactic shock, hypotension, throat tightness, bradycardia, shortness of breath, nausea, abdominal cramping, diaphoresis, hives, rash, itching; and numbness of face, lips and eyes [see Contraindications (4), (5.1)].

Neurological reactions: seizures, headache.

Vasovagal reactions: dizziness, loss of consciousness, nausea, diaphoresis, syncope and hypotension (generally self-limiting).

Other: nausea, vomiting, flushing, hypertension, urge to defecate, diarrhea, sneezing.

7 DRUG INTERACTIONS

7.1 Drugs that Affect Gallbladder Motility or Contractile Response

Drugs that may stimulate or inhibit gallbladder motility or contractile response may interfere with the response to sincalide. Consider discontinuing these drugs prior to administration of Sincalide for Injection, when used to stimulate contraction of the gallbladder.

8 USE IN SPECIFIC POPULATIONS

8.1 Pregnancy

Risk Summary

Based on limited human data and mechanism of action, sincalide may cause preterm labor or spontaneous abortion [see Warnings and Precautions (5.4)]. Available data with Sincalide for Injection are insufficient to establish a drug-associated risk of major birth defects, miscarriage or adverse maternal or fetal outcomes. In animal embryo-fetal development studies in which sincalide was administered to hamsters and rats during the period of organogenesis, no effects were seen at doses comparable to the maximum recommended clinical dose on a mg/kg basis. However, in a prenatal development study in which rats were administered sincalide during organogenesis through parturition, decreased weight gain and developmental delays were observed at a dose 122 times higher than the maximum recommended human dose based on body surface area.

The estimated background risk of major birth defects and miscarriage for the indicated population is unknown. All pregnancies have a background risk of birth defect, loss, or other adverse outcomes. In the U.S. general population, the estimated background risk of major birth defects and miscarriage in clinically recognized pregnancies is 2 to 4% and 15 to 20%, respectively.

Data

Animal Data

There were no effects on embryo-fetal development in hamsters when sincalide was administered subcutaneously at 250 or 750 ng/kg during organogenesis (Gestation Days 7 to 13) at doses up to 0.8 times the maximum recommended dose of 120 ng/kg on a body surface area basis. No effects on embryo-fetal development were observed in Sprague-Dawley rats at subcutaneous doses of 250, 450, or 750 ng/kg from Gestation Days 6 to16, representing 1.0 time the maximum recommended human dose on a body surface area basis. In a separate study at a higher dose of 90 mcg/kg administered subcutaneously to CFY rats from Gestation Day 10 through parturition (representing 122 times the maximum recommended human dose on a body surface area basis), offspring showed decreased growth, behavioral changes, and developmental delays.

8.2 Lactation

Risk Summary

There are no data regarding the presence of sincalide in human or animal milk, the effects on the breastfed infant, or the effects on milk production. The developmental and health benefits of breastfeeding should be considered along with the mother's clinical need for Sincalide for Injection and any potential adverse effect on the breastfed infant from Sincalide for Injection or from the underlying condition.

8.4 Pediatric Use

The safety and effectiveness in pediatric patients have not been established.

8.5 Geriatric Use

Clinical studies of Sincalide for Injection did not include sufficient numbers of subjects aged 65 and over to determine whether they respond differently from younger subjects.

10 OVERDOSAGE

In the event of an overdose, symptoms related to vagal stimulation, such as gastrointestinal symptoms (abdominal cramps, nausea, vomiting and diarrhea), hypotension with dizziness or fainting may occur. Overdosage symptoms should be treated symptomatically and should be of short duration.

A single bolus intravenous injection of 0.05 mcg/kg (approximately 2 to 3 times the human dose of 0.02 mcg/kg), sincalide caused hypotension and bradycardia in dogs. In addition, higher doses injected intravenously once or repeatedly in dogs caused syncope and ECG changes (approximately 5 times the human dose of 0.02 mcg/kg). These effects were attributed to sincalide-induced vagal stimulation in that all were prevented by pretreatment with atropine or bilateral vagotomy.

11 DESCRIPTION

Sincalide for Injection is a cholecystopancreatic-gastrointestinal hormone for parenteral administration. The agent is a synthetically-prepared C-terminal octapeptide of cholecystokinin.

Each single-dose vial of sincalide provides a sterile nonpyrogenic lyophilized white powder consisting of 5 mcg sincalide with 30 mg arginine hydrochloride, 15 mg lysine hydrochloride, 170 mg mannitol, 4 mg methionine, 2 mg pentetic acid, 0.005 mcg polysorbate 20, 9 mg potassium phosphate dibasic, and 0.04 mg sodium metabisulfite.

The pH is adjusted to 6.0 to 8.0 with hydrochloric acid and/or sodium hydroxide prior to lyophilization. Sincalide is designated chemically as L-α-aspartyl-O-sulfo-L-tyrosyl-L-methionylglycyl-L-tryptophyl-L-methionyl- L-α-aspartyl-L-phenylalaninamide. Graphic formula:

12 CLINICAL PHARMACOLOGY

12.1 Mechanism of Action

When injected intravenously, sincalide stimulates gallbladder contraction and reduction in size. The evacuation of bile that results is similar to that which occurs physiologically in response to endogenous cholecystokinin. Sincalide also stimulates pancreatic secretion and intestinal motility causing pyloric contraction and slows gastric emptying.

Concurrent administration of sincalide with secretin increases both the volume of pancreatic secretion and the out-put of bicarbonate and enzymes. This combined effect of secretin and sincalide permits the assessment of specific pancreatic function through measurement and analysis of the duodenal aspirate.

12.2 Pharmacodynamics

Following an intravenous (bolus) injection of 0.02 mcg/kg of sincalide, maximal contraction of the gallbladder occurred in 5 to 15 minutes. Sincalide reduced gallbladder radiographic size by at least 40%, which is generally considered satisfactory contraction.

13 NONCLINICAL TOXICOLOGY

13.1 Carcinogenesis, Mutagenesis, Impairment of Fertility

Long-term studies in animals have not been performed to evaluate carcinogenic or mutagenic potential, or possible impairment of fertility in males or females.

16 HOW SUPPLIED/STORAGE AND HANDLING

Sincalide for Injection is supplied as 5 mcg of sincalide as a lyophilized white powder for reconstitution in a single-dose vial; in packages of 10 vials as follows:

Product Code | Unit of Sale | Strength | Each
579105 | NDC 63323-579-05 Unit of 10 | 5 mcg per vial | NDC 63323-579-01 Single-Dose Vial

Store at 25° C (77° F); excursions permitted to 15-30° C (59-86° F) [See USP Controlled Room Temperature].

17 PATIENT COUNSELING INFORMATION

Anaphylaxis, Anaphylactic Shock and Other Serious Hypersensitivity Reactions

Inform patients that serious hypersensitivity reactions, including anaphylaxis and anaphylactic shock have been reported during or following administration of Sincalide for Injection. Advise patients to report immediately to a healthcare provider if they experience symptoms of a hypersensitivity reaction [see Warnings and Precautions (5.1)].

Gastrointestinal Adverse Reactions

Advise patients that Sincalide for Injection may cause transient gastrointestinal symptoms [see Warnings and Precautions (5.3)].

Pregnancy

Advise pregnant women of the potential risk for preterm labor and spontaneous abortion [see Warnings and Precautions (5.4), Use in Specific Populations (8.1)].

Rx only

Manufactured by:

Lake Zurich, IL 60047
www.fresenius-kabi.com/us

451763A /Revised: October 2023

Principal Display Panel – Sincalide for Injection 5 mcg per vial – Tray Label

NDC 63323-579-05 Rx only

Sincalide
for Injection

5 mcg per vial

For Intravenous use

10 Single-Dose Vials
Discard Unused Portion

Principal Display Panel – Sincalide for Injection 5 mcg per vial – Vial Label

NDC 63323-579-01 Rx only

Sincalide
for Injection

5 mcg per vial

For Intravenous use
Single-Dose Vial
Discard Unused Portion